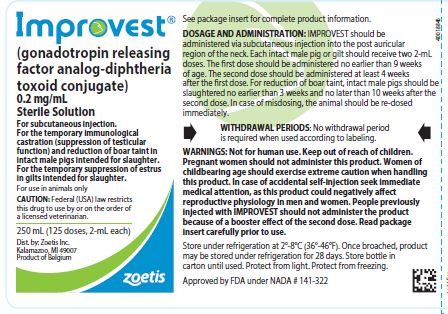 DRUG LABEL: Improvest
NDC: 54771-1534 | Form: SOLUTION
Manufacturer: Zoetis Inc.
Category: animal | Type: PRESCRIPTION ANIMAL DRUG LABEL
Date: 20200505

ACTIVE INGREDIENTS: GONADOTROPIN RELEASING FACTOR ANALOG-DIPHTHERIA TOXOID CONJUGATE 0.2 mg/1 mL
INACTIVE INGREDIENTS: DIETHYLAMINOETHYL-DEXTRAN HYDROCHLORIDE 150 ug/1 mL; CHLOROCRESOL

Improvest®

(gonadotropin releasing factor analog-diphtheria toxoid conjugate)
0.2 mg/mL
Sterile Solution for Injection

CAUTION

Federal (USA) law restricts this drug to use by or on the order of a licensed veterinarian.

DESCRIPTION

IMPROVEST (gonadotropin releasing factor analog-diphtheria toxoid conjugate) is a sterile solution for subcutaneous injection. Each mL contains 0.2 mg gonadotropin releasing factor analog-diphtheria toxoid conjugate, 150 mg of diethylaminoethyl-dextran hydrochloride, 1 mg chlorocresol, sodium hydroxide as needed to adjust pH and water for injection.

INDICATIONS FOR USE: For the temporary immunological castration (suppression of testicular function) and reduction of boar taint in intact male pigs intended for slaughter.
For the temporary suppression of estrus in gilts intended for slaughter.

DOSAGE AND ADMINISTRATION

IMPROVEST should be administered via subcutaneous injection into the post auricular region of the neck. A safety injector should be used, preferably one which has a dual safety system providing both a needle guard and a mechanism to prevent accidental operation of the trigger. The bottle is to be punctured by a vaccinator spike. Use bottle within 28 days of first puncture and puncture a maximum of twice. Each intact male pig or gilt should receive two 2-mL doses of IMPROVEST. The first dose should be administered no earlier than 9 weeks of age. The second dose should be administered at least 4 weeks after the first dose. For reduction of boar taint, intact male pigs should be slaughtered no earlier than 3 weeks and no later than 10 weeks after the second dose. In case of misdosing, the animal should be re-dosed immediately

CONTRAINDICATIONS

Do not use IMPROVEST in intact male pigs or gilts intended for breeding because of the disruption of reproductive function.
Not approved for use in barrows, cull boars, or sows

WARNINGS AND PRECAUTIONS

WITHDRAWAL PERIODS:

No withdrawal period is required when used according to labeling.

Not for Human Use. Keep Out of Reach of Children.

USER SAFETY WARNINGS:

Warning for person administering IMPROVEST

Accidental self-injection could affect reproductive physiology of both men and women and may adversely affect pregnancy and fertility. Pregnant women should not administer this product. Women of childbearing age should exercise extreme caution when handling this product. Special care should be taken to avoid accidental self-injection and needle stick injury when administering the product. Protective clothing including, but not limited to, safety glasses and gloves should be worn. Use a safety injector, preferably one which has a dual safety system providing both a needle guard and a mechanism to prevent accidental operation of the trigger. In case of eye contact, rinse immediately with copious amounts of water. In case of skin contact, wash immediately with soap and water. The product should be stored safely out of the reach of children. As a reminder, it is the prescribing veterinarian’s responsibility to inform drug administrators of the user safety warnings associated with IMPROVEST.

Advice to the user in the event of accidental self-injection

In the event of accidental self-injection, wash the injury thoroughly with clean running water. Seek prompt medical attention and take the package leaflet with you. Do not administer the product, and/or any other product with a similar action, in the future.

Advice to the physician

Accidental self-injection could affect reproductive physiology of both men and women and may adversely affect pregnancy and fertility. If self-injection with IMPROVEST is suspected, reproductive physiology should be monitored by assay of testosterone or estrogen levels (as appropriate).

The risk of a physiological effect is greater after a second or subsequent accidental injection than after a first injection. The patient should be advised not to administer IMPROVEST, and/or any other product with a similar action, in the future.

To report suspected adverse events, for technical assistance, or to obtain a copy of the safety data sheet (SDS), contact Zoetis 1-888-963-8471.
For additional information about adverse drug experience reporting for animal drugs, contact the FDA at 1-888-FDA-VETS or online at www.fda.gov/reportanimalae.

ANIMAL SAFETY WARNINGS AND PRECAUTIONS

Subcutaneous injection in intact male pigs and gilts can cause a transient local injection site reaction that may result in trim loss at slaughter.

ADVERSE REACTIONS

Preapproval Experience: The field study observations from field effectiveness studies were consistent with the observations made during the target animal safety studies of transient inflammation at the injection sites. IMPROVEST did not cause unusual clinical signs or an unexpected frequency or severity of injection site reactions, apart from the mild anaphylactoidtype reactions immediately following the first injection. Otherwise adverse events, as reported, were not uniquely attributable to IMPROVEST.
Postapproval Experience: (December 2013) The following adverse events are based on voluntary, post approval reporting in male pigs. Not all adverse events are reported to FDA/CVM. It is not always possible to reliably estimate the adverse event frequency or establish a causal relationship to product exposure using these data. In some cases anaphylactoid / anaphylactic-type reactions have been observed within a few minutes after the first administration of IMPROVEST with duration up to 30 minutes. Clinical signs may include dyspnea, cyanosis, ataxia, emesis or hypersalivation. Most animals recovered. In some cases, death has been reported as an outcome.

TARGET ANIMAL SAFETY:

Margin of Safety

The safety of two doses of IMPROVEST was evaluated in intact male swine. Thirty 9-week old intact boars received two subcutaneous doses of IMPROVEST in the same location 14 days apart. The boars received one of three treatments: Saline Control (12-mL), IMPROVEST at the intended dose (2-mL, 1X), or IMPROVEST at 6 times the intended dose (12-mL, 6X).
Boars were clinically monitored daily. In addition, observation and measurement of injection sites, body weight, quantitative feed consumption, hematology, and clinical chemistry analyses were also obtained. A complete postmortem examination was conducted on each boar 14 days after the second injection. IMPROVEST, administered subcutaneously at the label dose (2-mL) resulted in mild transient injection site reactions at the 1X dose and caused clinical signs of systemic inflammation at 6X the intended dose.
The signs of inflammation included depression, stiffness of the neck lasting up to five days, reduction in feed intake, and lower body weights. Multiple swollen joints and associated lameness, which may be signs of systemic inflammation, were observed in one 6X boar. Evaluation of blood work revealed increased white blood cell counts (eosinophilia and eutrophilia);
slight increases in total serum protein (above normal reference range in 50% of the 6X boars) and globulin (above the normal reference range in 40% of the 6X boars); and slight decreases in serum albumin in 6X boars. Injection sites for the 6X boars showed clinically detectable firmness persisting in all animals for 14 days after the second injection. Pain and sensitivity at the injection site persisted for up to five days, and erythema and heat were more prominent in the 6X boars than in the 1X boars. Mild to moderate chronic inflammation and discoloration in the subcutaneous tissues at the injection site were observed. In all IMPROVEST treated boars, atrophy of testes, prostate, and bulbourethral glands were observed as expected consequences associated with the intended effect of the drug. At the label 2-mL dose, IMPROVEST may cause transient injection site inflammation.

Injection site safety was evaluated following the injection of IMPROVEST into healthy 17-week old boars. The treated boars received two 2-mL doses of IMPROVEST into the same injection site location 28 days apart, while the control boars received saline. Daily monitoring included clinical evaluation and observation and measurement of injection sites. Two days after the second injection, postmortem observations of injection sites were conducted. All clinical signs of observable injection site swelling were resolved within 24 hours, and pain on palpation resolved by 48 hours post-injection. Firmness persisted for up to 11 days after the first injection in 10% of boars. Gross injection site alterations consisted of subcutaneous edema with tan or red discoloration. Two 2-mL injections of IMPROVEST, administered 28 days apart into the same location resulted in transient injection site reactions following each injection and resulted in discoloration of tissue at the injection site which was observable approximately 48 hours after the second injection.

Field Safety

During the conduct of the nine location field effectiveness study in male pigs, IMPROVEST did not cause unusual clinical signs or an unexpected frequency or severity of injection site reactions. The field safety observations from this study were consistent with the observations made during the target animal safety studies of transient inflammation at the injection sites. Adverse events, as reported, were not uniquely attributable to IMPROVEST. Similarly, during the conduct of field effectiveness studies in gilts, IMPROVEST did not cause unusual clinical signs or an unexpected frequency or severity of injection site reactions.

EFFECTIVENESS

IMPROVEST is an injectable sterile solution containing an incomplete analog of natural gonadotropin releasing factor (GnRF) conjugated to diphtheria toxoid in an adjuvanted formulation. Immunization with a two dose regimen of IMPROVEST, with a four week interval between doses, stimulates the pig’s immune system to produce antibodies which can neutralize its own GnRF. Pigs given an initial dose of IMPROVEST are immunologically primed but do not produce sufficient antibodies to have any physiological effect. Following receipt of the second dose, the pig’s immune system responds with a strong antibody response. These antibodies bind to and neutralize circulating GnRF in the bloodstream. Neutralization of GnRF blocks the hypothalamic-pituitarygonadal endocrine axis, thereby temporarily suppressing gonadal function, including both sex hormone production and reproductive capability in intact males; and temporarily suppressing estrus in gilts.
In male pigs, evidence of temporary immunological castration was provided in a series of studies showing that within 1-2 weeks after the second injection of IMPROVEST, anti-GnRF antibody levels increase significantly. With this rise in anti-GnRF antibodies, the levels of gonadal sex hormones were substantially reduced, the size of the testes, and spermatogenesis suppressed, as was the expression of typical male behaviors (aggression and sexual, e.g., mounting). Full immunological castration (suppression of testicular function) was demonstrated to last from 3 to 10 weeks after the second dose.

IMPROVEST injected boars will start to return to full reproductive function at a variable period after this time, as evidenced by increases in male sex hormones, testicle size, and intact male behavior.

Evidence to assess the acceptability of pork from IMPROVEST treated male pigs was provided through a series of consumer taste panels using consumers deemed sensitive to the taste of ”tainted” meat. The presence of boar taint was evaluated on the basis of pork aroma and flavor and not by chemical analysis. Four consumer taste panel studies were conducted to demonstrate the difference of pork generated from IMPROVEST treated boars and intact boars. A surgically castrated male group was not evaluated during these studies. In these four studies, 767 sensitive consumers evaluated cooked pork loin samples from IMPROVEST treated and intact boars. These pigs were raised to market weight, injected with IMPROVEST as per product labelling and slaughtered 3 to 10 weeks after receipt of the second IMPROVEST injection. The consumers found the aroma and flavor of pork from the IMPROVEST injected pigs to be more acceptable than from the intact boars in all four studies.
In gilts, evidence of temporary suppression of estrus was provided in several studies showing that after the second injection of IMPROVEST, anti-GnRF antibody levels increased significantly, the weight of the ovaries was significantly decreased, and the percentage of gilts with visible follicles was low. In a study specifically evaluating estrus detection (standing response in the presence of a mature boar), IMPROVEST was effective in suppressing estrus from 2 weeks to 10 weeks after the second dose

STORAGE INFORMATION

Store under refrigeration at 2°-8°C (36°-46°F). Once broached, product may be stored under refrigeration for 28 days. Store bottle in carton until used. Protect from light. Protect from freezing.

HOW SUPPLIED

IMPROVEST is available in a 250 mL bottle.

Approved by FDA under NADA # 141-322
zoetis
Distributed by:
Zoetis Inc.
Kalamazoo, MI 49007
Revised: January 2020
40018847